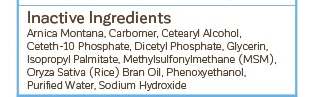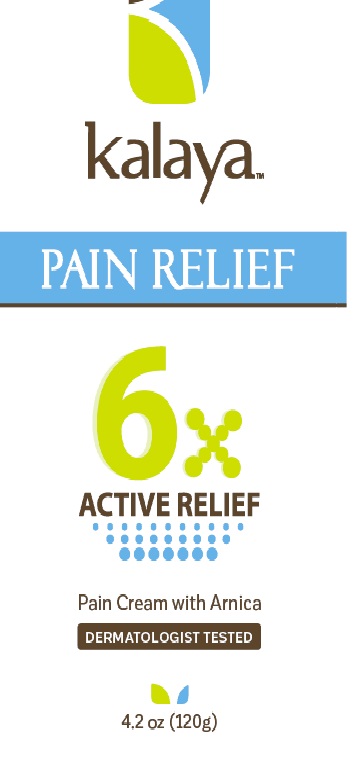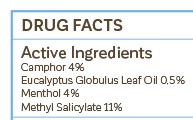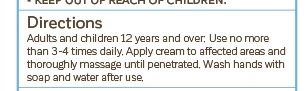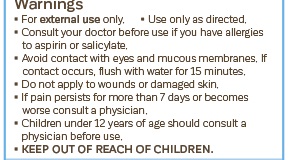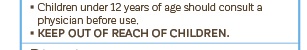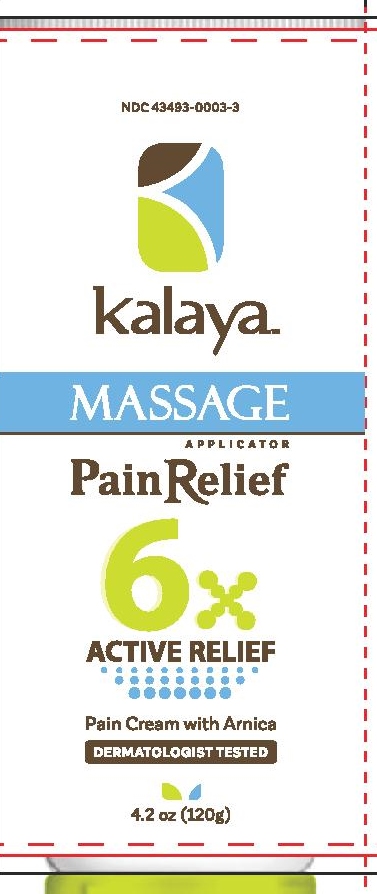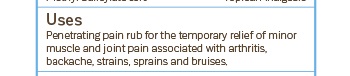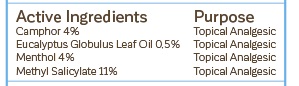 DRUG LABEL: Kalaya Pain Relief 6X with Arnica
NDC: 43493-0003 | Form: CREAM
Manufacturer: Avaria Health & Beauty Corp
Category: otc | Type: HUMAN OTC DRUG LABEL
Date: 20251008

ACTIVE INGREDIENTS: METHYL SALICYLATE 11 g/100 g; MENTHOL 4 g/100 g; CAMPHOR (NATURAL) 4 g/100 g; EUCALYPTUS OIL 0.5 g/100 g
INACTIVE INGREDIENTS: WATER; RICE BRAN OIL; CETYL ALCOHOL; ISOPROPYL PALMITATE; SODIUM HYDROXIDE; GLYCERIN; ARNICA MONTANA; CARBOMER COPOLYMER TYPE A; CETETH-10 PHOSPHATE; DIHEXADECYL PHOSPHATE; DIMETHYL SULFONE; DIETHYLENE GLYCOL MONOPHENYL ETHER

Avaria
Kalaya- 3 package put ups. Two tubes and one roller applicator.